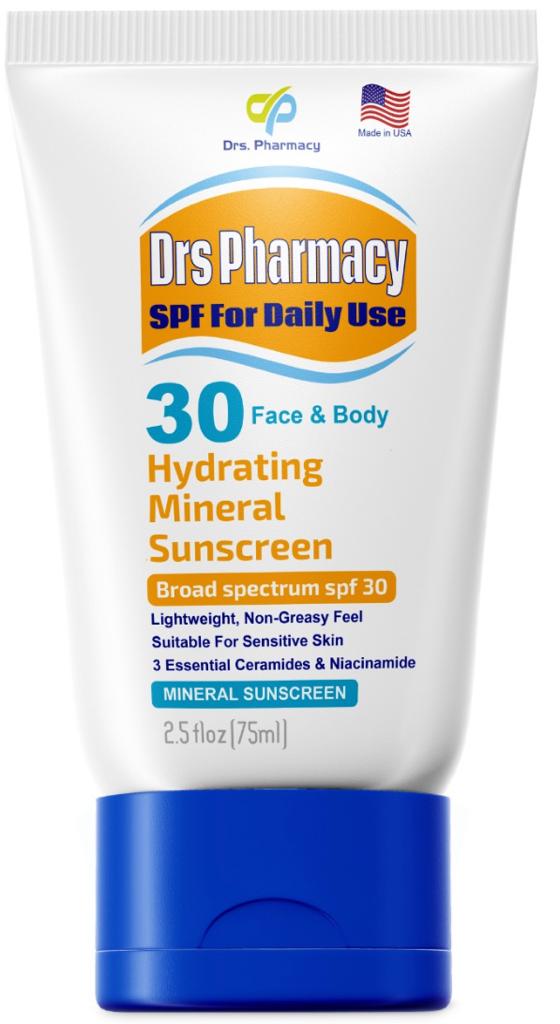 DRUG LABEL: Drs. pharmacy sunscreen SPF 30 (Physical Filters)
NDC: 80489-887 | Form: CREAM
Manufacturer: OL PHARMA TECH LLC. (Drs. Pharmacy)
Category: otc | Type: HUMAN OTC DRUG LABEL
Date: 20260106

ACTIVE INGREDIENTS: ZINC OXIDE 6 g/100 g; TITANIUM DIOXIDE 2.48 g/100 g
INACTIVE INGREDIENTS: GLYCERIN; BEHENYL ALCOHOL; WATER; EDETATE DISODIUM ANHYDROUS; PEG-20 METHYL GLUCOSE SESQUISTEARATE; CYCLOMETHICONE; CARBOMER COPOLYMER TYPE A; ISOPROPYL ISOSTEARATE; XANTHAN GUM; SODIUM HYDROXIDE; PHENOXYETHANOL; METHYL GLUCETH-20; MEDIUM-CHAIN TRIGLYCERIDES; PROPYLENE GLYCOL; METHYL GLUCOSE SESQUISTEARATE

ACTIVE INGREDIENTS

Titanium dioxide 2.48 % Zinc oxide 6%

PURPOSE

Sunscreen Agent

USES

• helps prevent sunburn
• if used as directed with other sun protection measures (see Directions), decreases the risk of skin cancer and early skin aging caused by the sun.

WARNINGS

For external use only

Do not use

on damaged or broken skin

DOSAGE AND ADMINISTRATION

- apply liberally 15 minutes before sun exposure.
- reapply after 80 minutes of swimming or sweating immediately after towel drying at least every 2 hours Sun Protection Measures.
- Spending time in the sun increases your risk of skin cancer and early skin aging. To decrease this risk, regularly use a sunscreen with a broad spectrum SPF value of 15 or higher and other sun protection measures including:
- limit time in the sun, especially from 10 a.m. – 2 p.m. wear long-sleeved shirts, pants, hats, and sunglasses
- children under 6 months: Ask a doctor

When using this product

keep out of eyes. Rinse with water to remove it

Stop use and ask a doctor

if rash occurs

Keep out of reach of children

If product is swallowed, get medical help or contact a Poison Control Center right away.

Inctive ingredients

Water, Carbomer,capric/caprylic Triglyceride, Glycerin, Sodium Hydroxide, Propylene Glycol, Xanthan Gum, methyl glycose sesquistearate,PEG-20 methyl glycose sesquistearate, Cyclomethicone, Behenyl alcohol, Isopropyl isostearate, phenoxyethanol, Methyl Gluceth-20, Disodium EDTA.

other information

protect this product from excessive heat and direct sunlight

Questions

www.drspharmacyusa.com